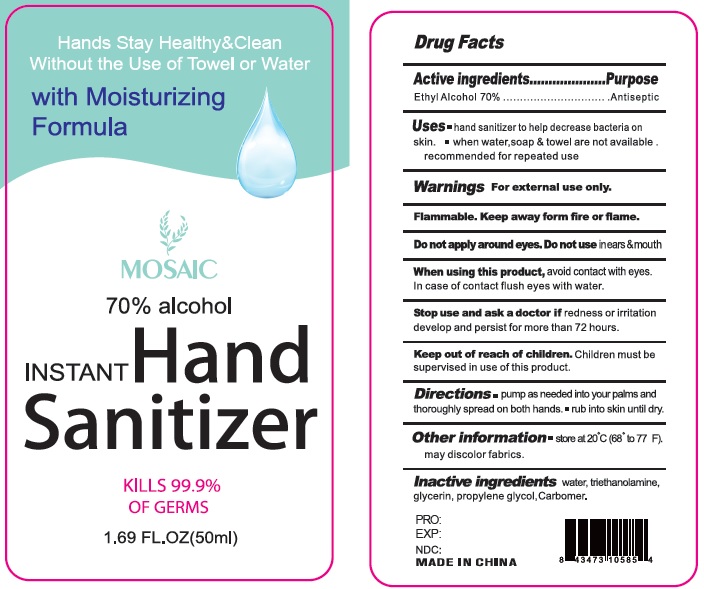 DRUG LABEL: MOSAIC Instant Hand Sanitizer
NDC: 52174-102 | Form: GEL
Manufacturer: Ningbo BST Clean And Care Products Co., Ltd
Category: otc | Type: HUMAN OTC DRUG LABEL
Date: 20200410

ACTIVE INGREDIENTS: alcohol 70 mL/100 mL
INACTIVE INGREDIENTS: WATER; PROPYLENE GLYCOL; ALOE VERA LEAF; CARBOMER 934; GLYCERIN; TROLAMINE

Drug facts

Active ingredient Purpose

Ethyl Alcohol 70% ... Antiseptic

PURPOSE

Hand sanitizer to help decrease bacteria on the skin.

KEEP OUT OF REACH OF CHILDREN

Children must be supervised in use of this product.

INDICATIONS AND USAGE

keep out of eyes

when water, soap and towel are not available

WARNINGS

For external use only.
Flammable. Keep away from hear or flame.

Do not apply around eyes; Do not use in ears and mouth. When using this products, avoid contact with eyes. In case of contact, flush eyes with water.

Stop using and ask a doctor, if redness and irritation develop and persist for more than 72 hours.

OTHER INFORMATION: store at 20 ℃ (68 - 77 ℉), may discolor fabrics.

DOSAGE AND ADMINISTRATION

Pump as needed into your palms and thoroughly spread on both hands, and rub the skin until dry.

Children must be supervised in use of this product.

INACTIVE INGREDIENT

Water, triethanolamine, Glycerin, Propylene glycol, Carbomer